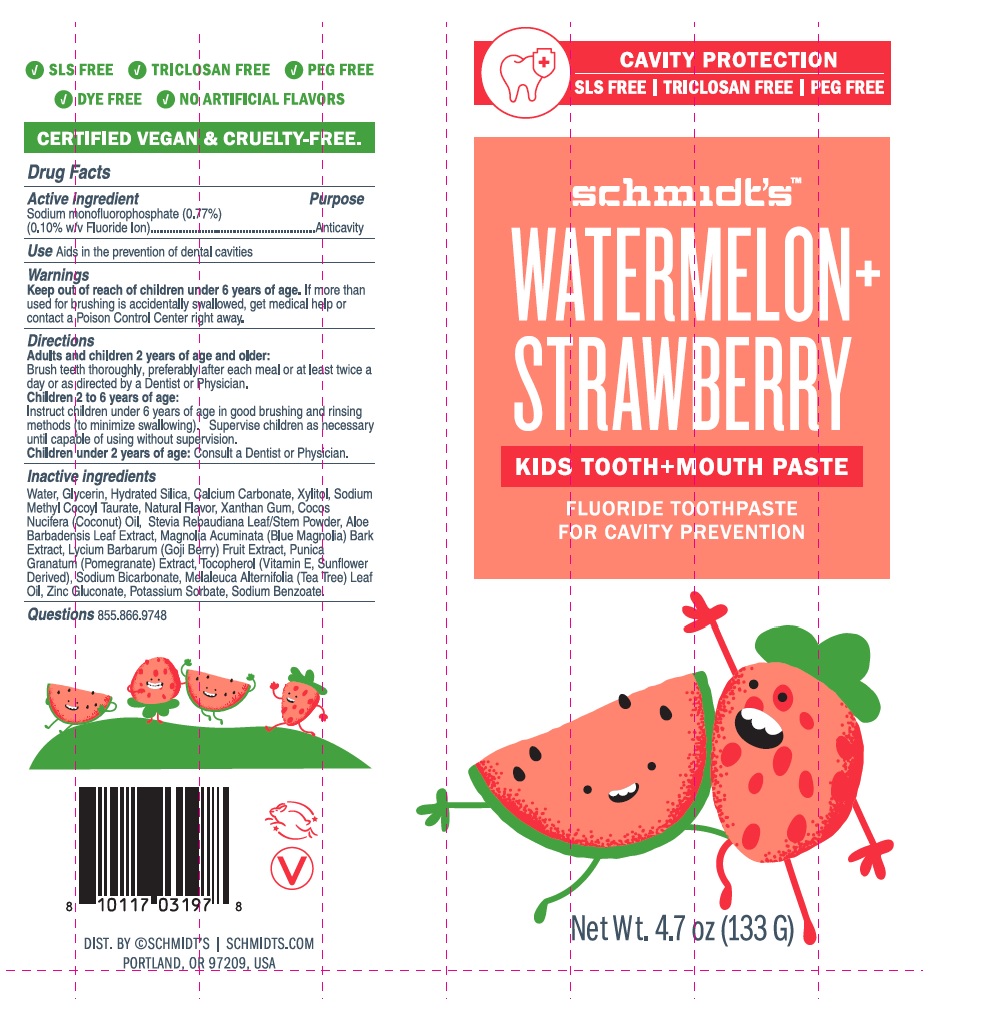 DRUG LABEL: Schmidts
NDC: 72916-310 | Form: PASTE, DENTIFRICE
Manufacturer: Schmidt's Naturals
Category: otc | Type: HUMAN OTC DRUG LABEL
Date: 20190612

ACTIVE INGREDIENTS: SODIUM MONOFLUOROPHOSPHATE 1.026 g/133 g
INACTIVE INGREDIENTS: WATER; GLYCERIN; HYDRATED SILICA; CALCIUM CARBONATE; XYLITOL; SODIUM METHYL COCOYL TAURATE; XANTHAN GUM; COCONUT OIL; STEVIA REBAUDIUNA LEAF; ALOE VERA LEAF; MAGNOLIA ACUMINATA BARK; LYCIUM BARBARUM FRUIT; POMEGRANATE; .ALPHA.-TOCOPHEROL; SODIUM BICARBONATE; TEA TREE OIL; ZINC GLUCONATE; POTASSIUM SORBATE; SODIUM BENZOATE

Schmidt's™-WATERMELON+STRAWBERRY KIDS TOOTH+MOUTH PASTE

Active ingredient

Sodium monofluorophosphate (0.77%)

(0.10% w/v Fluoride Ion)

Purpose

Anticavity

Use

Aids in the prevention of dental cavities

Warnings

Keep out of reach of children under 6 years of age. If more than used for brushing is accidentally swallowed, get medical help or contact a Poison Control Center right away.

Directions

Adults and children 2 years of age and older:

Brush teeth thoroughly, preferably after each meal or at least twice a day or as directed by a Dentist or Physician.

Children 2 to 6 years of age:

Instruct children under 6 years of age in good brushing and rinsing methods (to minimize swallowing). Supervise children as necessary until capable of using without supervision.

Children under 2 years of age: Consult a Dentist or Physician.

Inactive ingredients

Water, Glycerin, Hydrated Silica, Calcium Carbonate, Xylitol, Sodium Methyl Cocoyl Taurate, Natural Flavor, Xanthan Gum, Cocos Nucifera (Coconut) Oil, Stevia Rebaudiana Leaf/Stem Powder, Aloe Barbadensis Leaf Extract, Magnolia Acuminata (Blue Magnolia) Bark Extract, Lycium Barbarum (Goji Berry) Fruit Extract, Punica Granatum (Pomegranate) Extract, Tocopherol (Vitamin E, Sunflower Derived), Sodium Bicarbonate, Melaleuca Alternifolia (Tea Tree) Leaf Oil, Zinc Gluconate, Potassium Sorbate, Sodium Benzoate.

Questions

855.866.9748

CAVITY PROTECTION

SLS FREE | TRICLOSAN FREE | PEG FREE

FLUORIDE TOOTHPASTE FOR CAVITY PREVENTION

√DYE FREE √NO ARTIFICIAL FLAVORS

CERTIFIED VEGAN & CRUELTY-FREE.

DIST. BY ©SCHMIDT'S | SCHMIDTS.COM
PORTLAND, OR 97209, USA